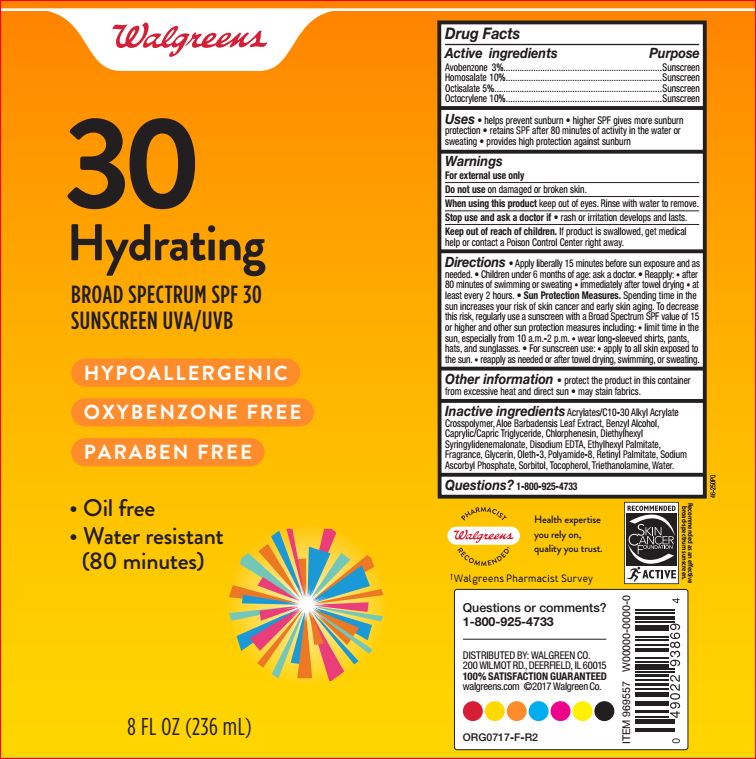 DRUG LABEL: Hydrating SPF 30
NDC: 0363-1124 | Form: LOTION
Manufacturer: Walgreens
Category: otc | Type: HUMAN OTC DRUG LABEL
Date: 20180430

ACTIVE INGREDIENTS: Avobenzone 3 g/100 mL; Homosalate 10 g/100 mL; Octisalate 5 g/100 mL; Octocrylene 10 g/100 mL
INACTIVE INGREDIENTS: CARBOMER INTERPOLYMER TYPE A (ALLYL SUCROSE CROSSLINKED); ALOE VERA LEAF; Benzyl Alcohol; MEDIUM-CHAIN TRIGLYCERIDES; Chlorphenesin; Diethylhexyl Syringylidenemalonate; EDETATE DISODIUM; Ethylhexyl Palmitate; Glycerin; Oleth-3; POLYAMIDE-8 (4500 MW); VITAMIN A PALMITATE; Sodium Ascorbyl Phosphate; Sorbitol; Tocopherol; TROLAMINE; water

Active ingredients Purpose
Avobenzone 3%.....................................................................Sunscreen
Homosalate 10%....................................................................Sunscreen
Octisalate 5%.........................................................................Sunscreen
Octocrylene 10%....................................................................Sunscreen

INDICATIONS AND USAGE

Uses • helps prevent sunburn • higher SPF gives more sunburn
protection • retains SPF after 80 minutes of activity in the water or
sweating • provides high protection against sunburn

Warnings
For external use only
Do not use on damaged or broken skin.
When using this product keep out of eyes. Rinse with water to remove.
Stop use and ask a doctor if • rash or irritation develops and lasts.

Other information • protect the product in this container
from excessive heat and direct sun • may stain fabrics.

Inactive ingredients Acrylates/C10-30 Alkyl Acrylate
Crosspolymer, Aloe Barbadensis Leaf Extract, Benzyl Alcohol,
Caprylic/Capric Triglyceride, Chlorphenesin, Diethylhexyl
Syringylidenemalonate, Disodium EDTA, Ethylhexyl Palmitate,
Fragrance, Glycerin, Oleth-3, Polyamide-8, Retinyl Palmitate, Sodium
Ascorbyl Phosphate, Sorbitol, Tocopherol, Triethanolamine, Water.